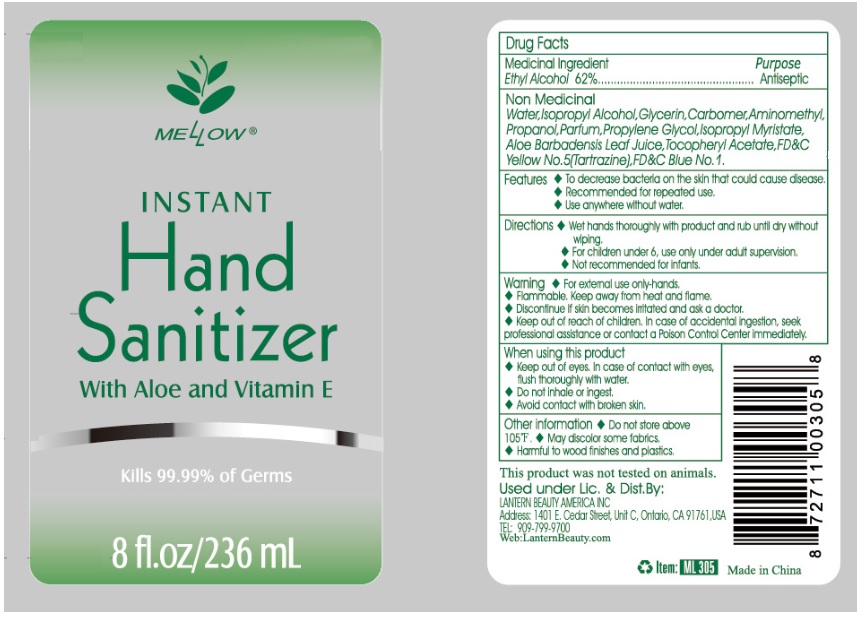 DRUG LABEL: MELLOW INSTANT Hand Sanitizer 8 oz
NDC: 70108-033 | Form: GEL
Manufacturer: Ashtel Studios, Inc
Category: otc | Type: HUMAN OTC DRUG LABEL
Date: 20200408

ACTIVE INGREDIENTS: ALCOHOL 62 mL/100 mL
INACTIVE INGREDIENTS: WATER; ISOPROPYL ALCOHOL; GLYCERIN; CARBOMER HOMOPOLYMER, UNSPECIFIED TYPE; AMINOMETHYLPROPANOL; PROPYLENE GLYCOL; ISOPROPYL MYRISTATE; ALOE VERA LEAF; .ALPHA.-TOCOPHEROL ACETATE; FD&C YELLOW NO. 5; FD&C BLUE NO. 1

MELLOW INSTANT Hand Sanitizer

Medicinal Ingredient

Ethyl Alcohol 62%

Purpose

Antiseptic

Non Medicinal

Water, Isopropyl Alcohol, Glycerin, Carbomer, Aminomethyl Propanol, Parfum, Propylene Glycol, Isopropyl Myristate, Aloe Barbadensis Leaf Juice, Tocopheryl Acetate, FD&C Yellow No. 5(Tartrazine), FD&C Blue No. 1

Features

♦ To decrease bacteria on the skin that could cause disease.

♦ Recommended for repeated use.

♦ Use anywhere without water.

Directions

♦ Wet hands thoroughly with product and rub until dry without wiping.

♦ For children under 6, use only under adult supervision.

♦ Not recommended for infants.

Warning

♦ For external use only-hands.

♦ Flammable. Keep away from heat and flame.

♦ Discontinue if skin becomes irritated and ask a doctor.

When using this product

♦ Keep out of eyes. In case of contact with eyes, flush thoroughly with water.

♦ Do not inhale or ingest.

♦ Avoid contact with broken skin.

♦ Keep out of reach of children. In case of accidental ingestion, seek professional assistance or contact a Poison Control Center immediately.

Other information

♦ Do not store above 105°F

♦ May discolor some fabrics,

♦ Harmful to wood finishes and plastics.

With Aloe and Vitamin E

Kills 99.99% of Germs

This product was not tested on animals.

Used under Lic. & Dist.By:

LANTERN BEAUTY AMERICA INC

Address: 1401 E, Cedar Street, Unit C, Ontario, CA 91761, USA

TEL: 909-799-9700

Web:LanternBeauty.com

Made in China